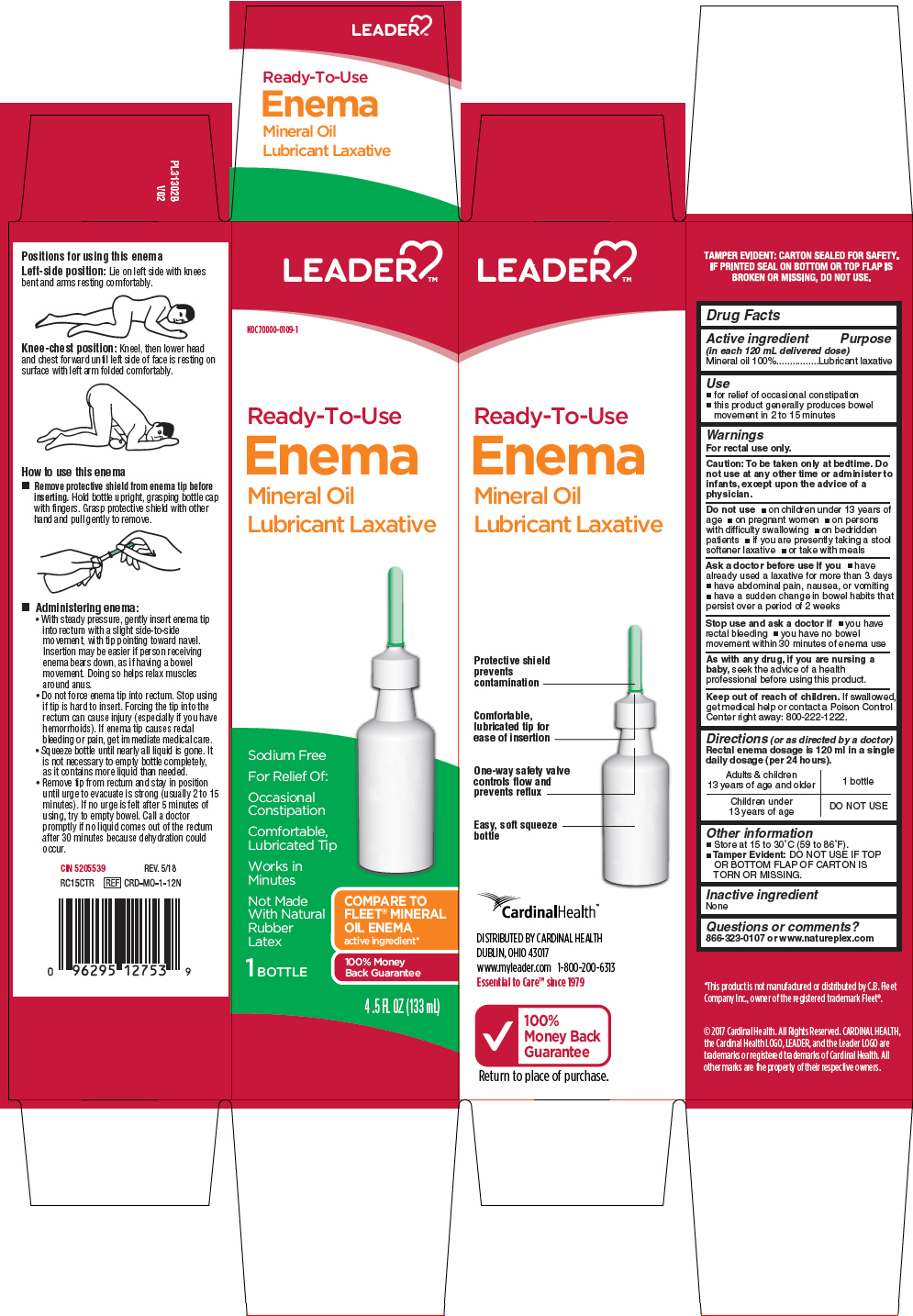 DRUG LABEL: Leader Ready to Use Mineral Oil 
NDC: 70000-0109 | Form: ENEMA
Manufacturer: Cardinal Health
Category: otc | Type: HUMAN OTC DRUG LABEL
Date: 20250929

ACTIVE INGREDIENTS: MINERAL OIL 118 g/118 mL

Leader® Ready to Use Mineral Oil Enema
Laxative

Drug Facts

Active ingredient (in each 118 mL delivered dose)

Mineral oil 100%

Purpose

Lubricant laxative

Uses

- for relief of occasional constipation
- for relief of fecal impaction
- for removal of residue after barium administration

Warnings

For rectal use only

Ask a doctor before use

- if you have abdominal pain, nausea, or vomiting
- if you have a sudden change in bowel habits that persists over a period of 2 weeks
- if you have already used a laxative for more than 1 week
- if constipation continues after one week of use, contact your doctor

Stop use and ask a doctor if

- you have rectal bleeding or no bowel movement within 15 minutes of using this product
- you need to use a laxative for more than one week

These symptoms may indicate a serious condition.

PREGNANCY OR BREAST FEEDING

If pregnant or breastfeeding, ask a health professional before use.

Keep out of reach of children to prevent accidental ingestion. If swallowed, get medical help or contact a Poison Control Center right away. (1-800-222-1222)

Directions

Single daily dose (per 24 hours).

adults & children 12 years and over | 1 bottle once daily
children 2 to under 12 years | 1/2 bottle once daily discard unused portion
children under 2 years | DO NOT USE

Other information

- store at 15°-30°C (59°-86°F)
- this product generally produces a bowel movement in 2 to 15 minutes

Inactive ingredients

none

Questions or comments?

1-866-323-0107

DISTRIBUTED BY CARDINAL HEALTH
DUBLIN, OHIO 43017

PRINCIPAL DISPLAY PANEL - 133 mL Bottle Carton

LEADER™

NDC 70000-0109-1

Ready-To-Use
Enema
Mineral Oil
Lubricant Laxative

Sodium Free

For Relief Of:

Occasional
Constipation

Comfortable,
Lubricated Tip

Works in
Minutes

Not Made
With Natural
Rubber
Latex

COMPARE TO
FLEET® MINERAL
OIL ENEMA
active ingredient*

1 BOTTLE

100% Money
Back Guarantee

4 .5 FL OZ (133 mL)